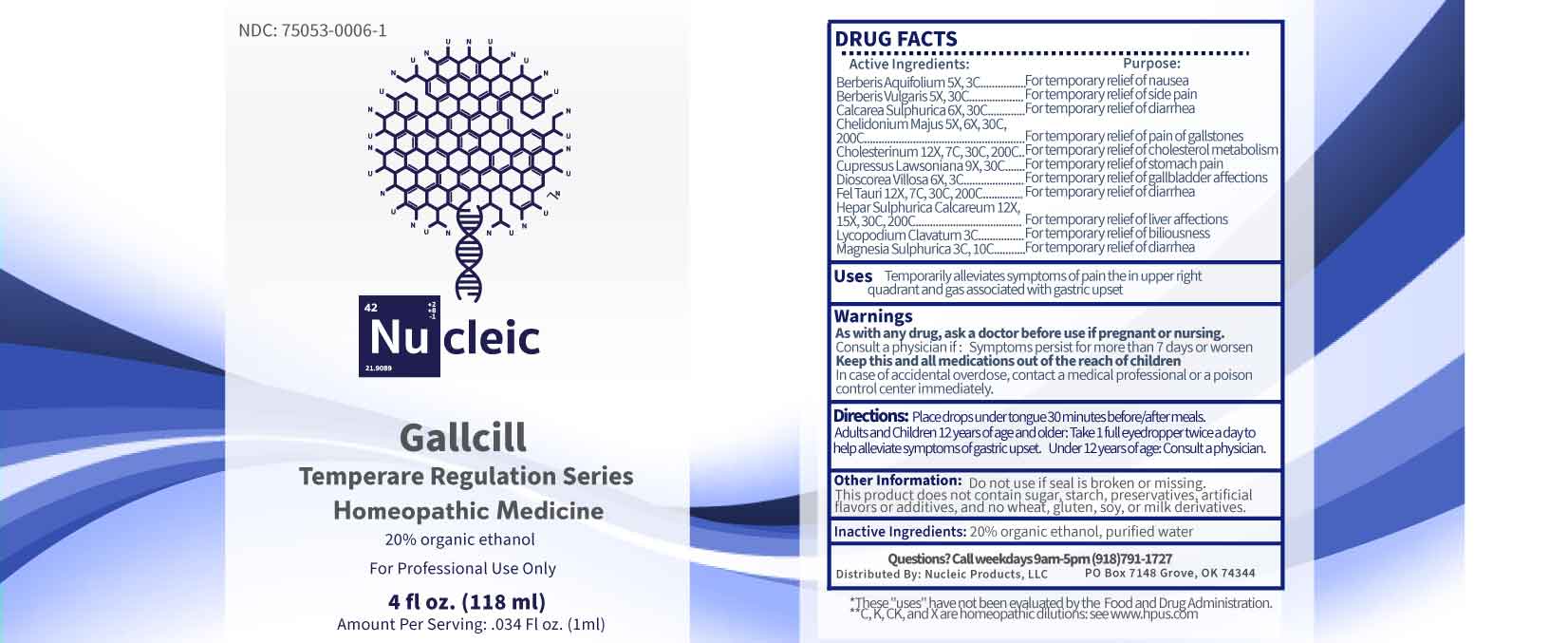 DRUG LABEL: Gallcill
NDC: 75053-0006 | Form: LIQUID
Manufacturer: Nucleic Products, LLC
Category: homeopathic | Type: HUMAN OTC DRUG LABEL
Date: 20251203

ACTIVE INGREDIENTS: CHELIDONIUM MAJUS WHOLE 5 [hp_X]/1 mL; BERBERIS AQUIFOLIUM ROOT BARK 5 [hp_X]/1 mL; BERBERIS VULGARIS ROOT BARK 5 [hp_X]/1 mL; DIOSCOREA VILLOSA TUBER 6 [hp_X]/1 mL; CALCIUM SULFATE ANHYDROUS 6 [hp_X]/1 mL; CHAMAECYPARIS LAWSONIANA FRUITING TWIG 9 [hp_X]/1 mL; CALCIUM SULFIDE 12 [hp_X]/1 mL; CHOLESTEROL 12 [hp_X]/1 mL; BOS TAURUS BILE 12 [hp_X]/1 mL; LYCOPODIUM CLAVATUM SPORE 3 [hp_C]/1 mL; MAGNESIUM SULFATE HEPTAHYDRATE 3 [hp_C]/1 mL
INACTIVE INGREDIENTS: WATER; ALCOHOL

DRUG FACTS:

ACTIVE INGREDIENTS:

Berberis Aquifolium 5X, 3C, Berberis Vulgaris 5X, 30C, Calcarea Sulphurica 6X, 30C, Chelidonium Majus 5X, 6X, 30C, 200C, Cholesterinum 12X, 7C, 30C, 200C, Cupressus Lawsoniana 9X, 30C, Dioscorea Villosa 6X, 3C, Fel Tauri 12X, 7C, 30C, 200C, Hepar Sulphurica Calcareum 12X, 15X, 30C, 200C, Lycopodium Clavatum 3C, Magnesia Sulphurica 3C, 10C.

PURPOSE:

Berberis Aquifolium – For temporary relief of nausea, Berberis Vulgaris - For temporary relief of side pain, Calcarea Sulphurica - For temporary relief of diarrhea, Chelidonium Majus - For temporary relief of pain of gallstones, Cholesterinum - For temporary relief of cholesterol metabolism, Cupressus Lawsoniana – For temporary relief of stomach pain, Dioscorea Villosa - For temporary relief of gallbladder affections, Fel Tauri - For temporary relief of diarrhea, Hepar Sulphurica Calcareum - For temporary relief of liver affections, Lycopodium Clavatum - For temporary relief of biliousness, Magnesia Sulphurica - diarrhea

USES:

Temporarily alleviates symptoms of pain in the upper right quadrant and gas associated with gastric upset.

*These "uses" have not been evaluated by the Food and Drug Administration.

**C, K, CK, and X are homeopathic dilutions: see www.hpus.com

WARNINGS:

As with any drug, ask a doctor before use if pregnant or nursing.

Consult a physician if: symptoms persist for more than 7 days or worsen.

Keep this and all medications out of the reach of children.

In case of accidental overdose, contact a medical professional or a Poison Control Center immediately.

Do not use if seal is broken or missing.

This Product does not contain sugar, starch, preservatives, artificial flavors or additives, and no wheat, gluten, soy, or milk derivatives.

KEEP OUT OF REACH OF CHILDREN:

In case of accidental overdose, contact a medical professional or a Poison Control Center immediately.

DIRECTIONS:

Place drops under tongue 30 minutes before/after meals. Adults and children 12 years and over: Take 1 full eyedropper twice a day to help alleviate symptoms of gastric upset. Under 12 years of age: Consult a physician.

INACTIVE INGREDIENTS:

20% organic ethanol, purified water

QUESTIONS:

Distributed by:
Nucleic Products, LLC

PO Box 7148

Grove, OK 74344

Call weekdays 9am-5pm (918)791-1727

PACKAGE LABEL DISPLAY:

NDC: 75053-0006-1

Nu cleic

Gallcill

Homeopathic Medicine

For Professional Use Only

4 fl oz. (118 ml)